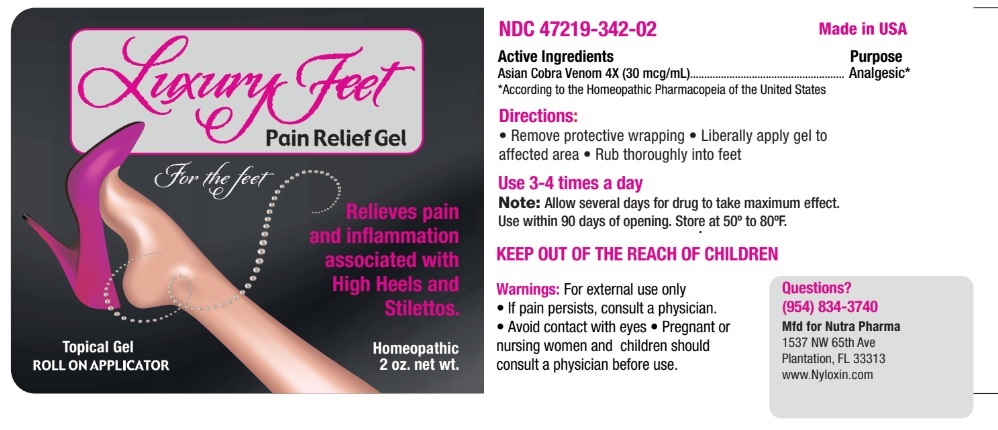 DRUG LABEL: Luxury feet
NDC: 47219-342 | Form: GEL
Manufacturer: Nutra Pharma Corporation
Category: homeopathic | Type: HUMAN OTC DRUG LABEL
Date: 20210715

ACTIVE INGREDIENTS: NAJA NAJA VENOM 4 [hp_X]/1 mL
INACTIVE INGREDIENTS: BENZALKONIUM CHLORIDE; ALCOHOL; HYDROXYPROPYL CELLULOSE (1600000 WAMW); PROPYLENE GLYCOL; SODIUM CHLORIDE

Active Ingredients

Asian Cobra Venom 4x

Purpose

Analgesic*
___________________________________________________________

*According to the Homeopathic Pharmacopeia of the United States

Uses:

Temporarily relieves joint pain associated with overuse and pain associated with arthritis.

Warnings:

- For external use only.

- If pain persist, consult a physician.

- Avoid contact with eyes.

- Pregnant or nursing women and children should consult a physician before use

Keep out of the reach of children

Directions for Use:

- Remove protective wrapping
- Liberally apply gel to the affected area and rub into joints.
- Use 3-4 time per day for the first week. Use as needed thereafter to relieve discomfort.
- Allow several days for drug to take maximum effect.

Other Information:

- Do not use if container seal is broken prior to opening.
- This product is intended for use in cases of recurring joint pain.
- This product is NOT intended to treat disease, it provides a temporary level of comfort, relief and a feeling of wellness.
- This product has been determined to be safe and effective for moderate to sever (Stage 2) chronic pain, as indicated by the Homeopathic Pharmacopeia of the United States.

ASK DOCTOR

- Pregnant or nursing women and children should consult a physician before use.

Inactive Ingredients:

Benzalkonium chloride, Ethanol, Methocel, Propylene glycol, Saline.

QUESTIONS

For more information visit: www.Nyloxin.com

Manufactured for Nutra Pharma

1537 NW 65th Avenue
Plantation, FL 33313

Questions?

(954) 834-3740